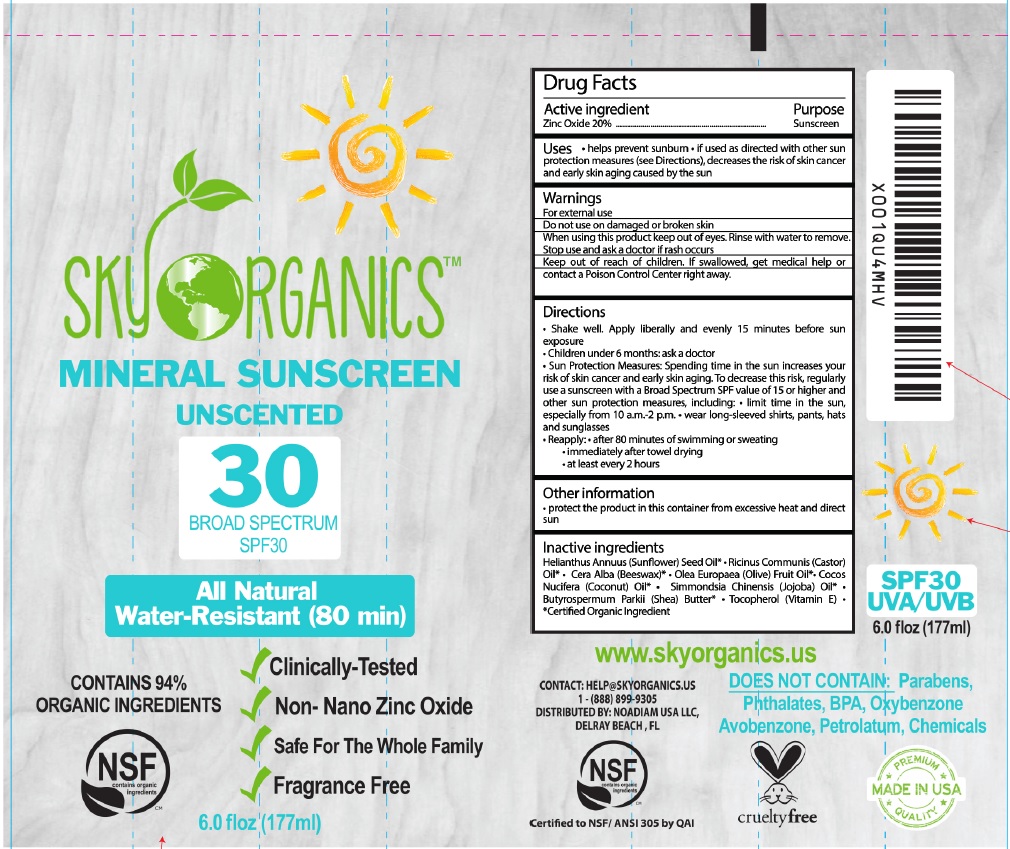 DRUG LABEL: SUNSCREEN
NDC: 62932-180 | Form: OINTMENT
Manufacturer: Private Label Select Ltd CO
Category: otc | Type: HUMAN OTC DRUG LABEL
Date: 20181118

ACTIVE INGREDIENTS: ZINC OXIDE 20 g/100 g
INACTIVE INGREDIENTS: OLEA EUROPAEA FRUIT VOLATILE OIL; HELIANTHUS ANNUUS SEED WAX; CASTOR OIL; YELLOW WAX; COCONUT OIL; SIMMONDSIA CHINENSIS SEED WAX; SHEA BUTTER; TOCOPHEROL

Sky Organics Mineral Sunscreen SPF30 177g